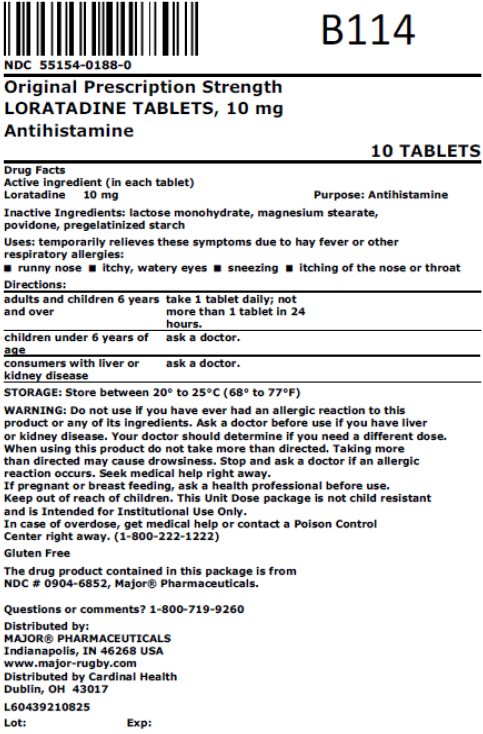 DRUG LABEL: Loratadine
NDC: 55154-0188 | Form: TABLET
Manufacturer: Cardinal Health 107, LLC
Category: otc | Type: HUMAN OTC DRUG LABEL
Date: 20250828

ACTIVE INGREDIENTS: LORATADINE 10 mg/1 1
INACTIVE INGREDIENTS: LACTOSE MONOHYDRATE; MAGNESIUM STEARATE; POVIDONE, UNSPECIFIED

Major Pharmaceuticals Allergy Drug Facts

Active ingredient (in each tablet)

Loratadine 10 mg

Purpose

Antihistamine

Uses

temporarily relieves these symptoms due to hay fever or other upper respiratory allergies:

- runny nose
- itchy, watery eyes
- sneezing
- itching of the nose or throat

Warnings

Do not use

if you have ever had an allergic reaction to this product or any of its ingredients

Ask a doctor before use if you have

liver or kidney disease. Your doctor should determine if you need a different dose.

When using this product

do not take more than directed. Taking more than directed may cause drowsiness.

Stop use and ask a doctor if

an allergic reaction to this product occurs. Seek medical help right away.

If pregnant or breast-feeding,

ask a health professional before use.

Keep out of reach of children.

In case of overdose, get medical help or contact a Poison Control Center right away. (1-800-222-1222)

Directions

adults and children 6 years and over | 1 tablet daily; not more than 1 tablet in 24 hours
children under 6 years of age | ask a doctor
consumers with liver or kidney disease | ask a doctor

Other information

- do not use if printed foil under cap is broken or missing
- store between 20° to 25°C (68° to 77°F)

Inactive ingredients

lactose monohydrate, magnesium stearate, povidone, pregelatinized starch

Questions or comments?

1-800-719-9260

Other Safety Information

Overbagged with 10 tablets per bag, NDC 55154-0188-0

This Unit Dose package is not child resistant and is intended for Institutional Use Only.

Gluten Free

The drug product contained in this package is from NDC # 0904-6852, Major® Pharmaceuticals

Distributed by:

MAJOR® PHARMACEUTICALS

Indianapolis, IN 46268 USA

www.major-rugby.com

Distributed By:

Cardinal Health

Dublin, OH 43017

L60439210825

LBLN0296-01

Rev. 03/25 | M-05 | Re-order No. 303078

Principal Display Panel

NDC 55154-0188-0

Original Prescription Strength

LORATADINE TABLETS, 10 mg

Antihistamine

10 TABLETS